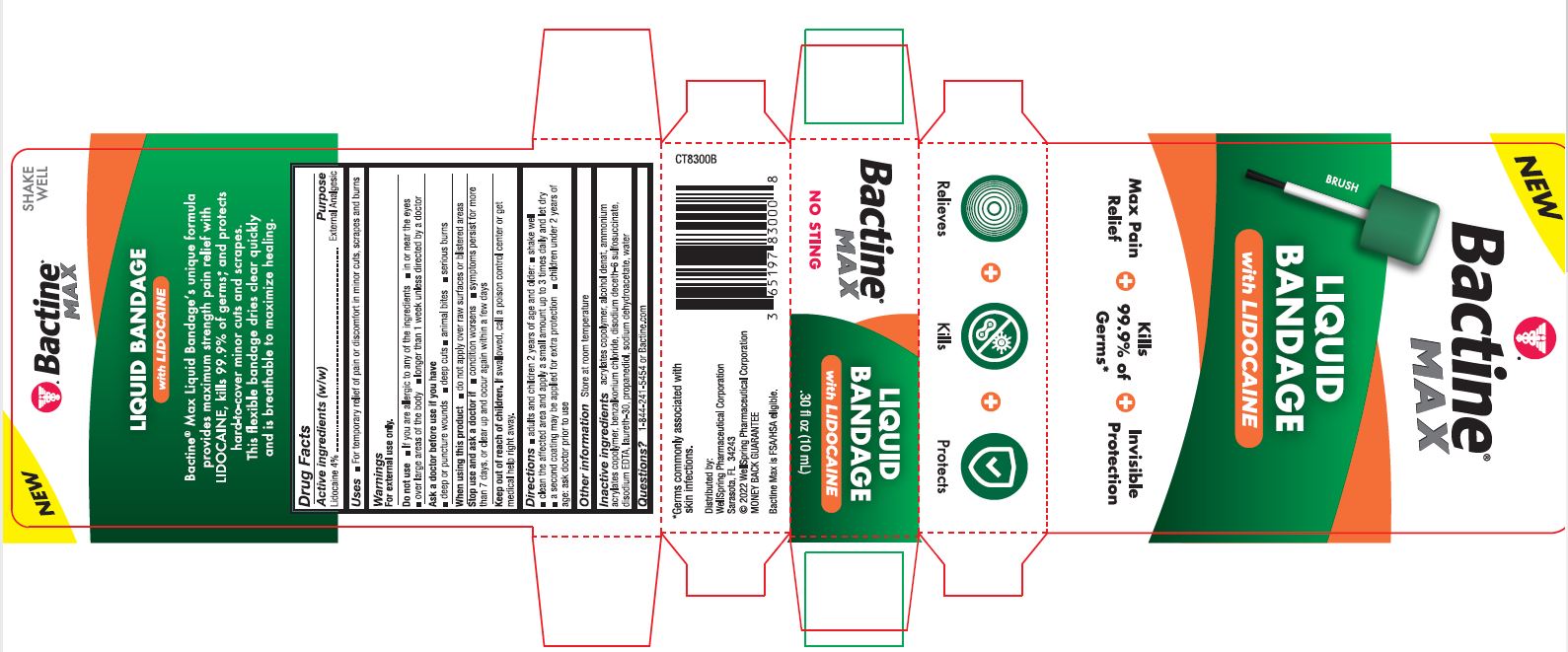 DRUG LABEL: Bactine Max
NDC: 65197-832 | Form: LIQUID
Manufacturer: WellSpring Pharmaceutical Corporation
Category: otc | Type: HUMAN OTC DRUG LABEL
Date: 20250108

ACTIVE INGREDIENTS: LIDOCAINE HYDROCHLORIDE 4 g/100 mL
INACTIVE INGREDIENTS: BUTYL ACRYLATE/METHYL METHACRYLATE/METHACRYLIC ACID COPOLYMER (18000 MW); ALCOHOL; BENZALKONIUM CHLORIDE; EDETATE DISODIUM; PROPANEDIOL; LAURETH-30; SODIUM DEHYDROACETATE; WATER

Bactine® Max Liquid Bandage

Active Ingredients (w/w)

Lidocaine 4%

Purpose

External Analgesic

Uses

For temporary relief of pain or discomfort in minor cuts, scrapes and burns.

Warnings

For external use only

Do not use

- If you are allergic to any of the ingredients
- in or near the eyes
- over large areas of the body
- longer than 1 week unless directed by a doctor

Ask a doctor before use if you have

- deep or puncture wounds
- deep cuts
- animal bites
- serious burns

When using this product

- do not apply over raw surfaces or blistered areas

Stop use and ask a doctor if

- condition worsens
- symptoms persist for more than 7 days, or clear up and occur again within a few days

Keep out of reach of children

- If swallowed, call a poison control center or get medical help right away.

Directions

- adults and children 2 years of age and older:
- shake well
- clean the affected area and apply a small amount up to 3 times daily and let dry
- a second coating may be applied for extra protection
- children under 2 years of age: ask doctor prior to use

Other information

Store at room temperature

Inactive ingredients

acrylates copolymer, alcohol denat, ammonium acrylates copolymer, benzalkonium chloride, disodium deceth-6 sulfosuccinate, disodium EDTA, laureth-30, propanediol, sodium dehydroacetate, water

Questions?

1-844-241-5454 or Bactine.com

Distributed by:

*Germs commonly associated with skin infections.

Distributed by:

WellSpring Pharmaceutical Corporation
Sarasota, FL 34243

© 2022 WellSpring Pharmaceutical Corporation
MONEY BACK GUARANTEE

Bactine Max is FSA/HSA eligible.

PACKAGE LABEL. PRINCIPAL DISPLAY PANEL

New

Bactine Max

Liquid Bandage with Lidocaine

Max Pain Relief

Kills 99% of Germs

Invisible Protection

Relieves Kills Protects

NO STING

SHAKE WELL

Bactine Max Liquid Bandage with Lidocaine

Back Panel

New

Bactine Max

Liquid Bandage with Lidocaine

SHAKE WELL

Bactine Max Liquid Bandageʼs unique formula provides maximum strength pain relief with LIDOCAINE, kills 99.9% of germs*, and protects hard-to-cover minor cuts and scrapes. This flexible bandage dries clear quickly and is breathable to maximize healing.